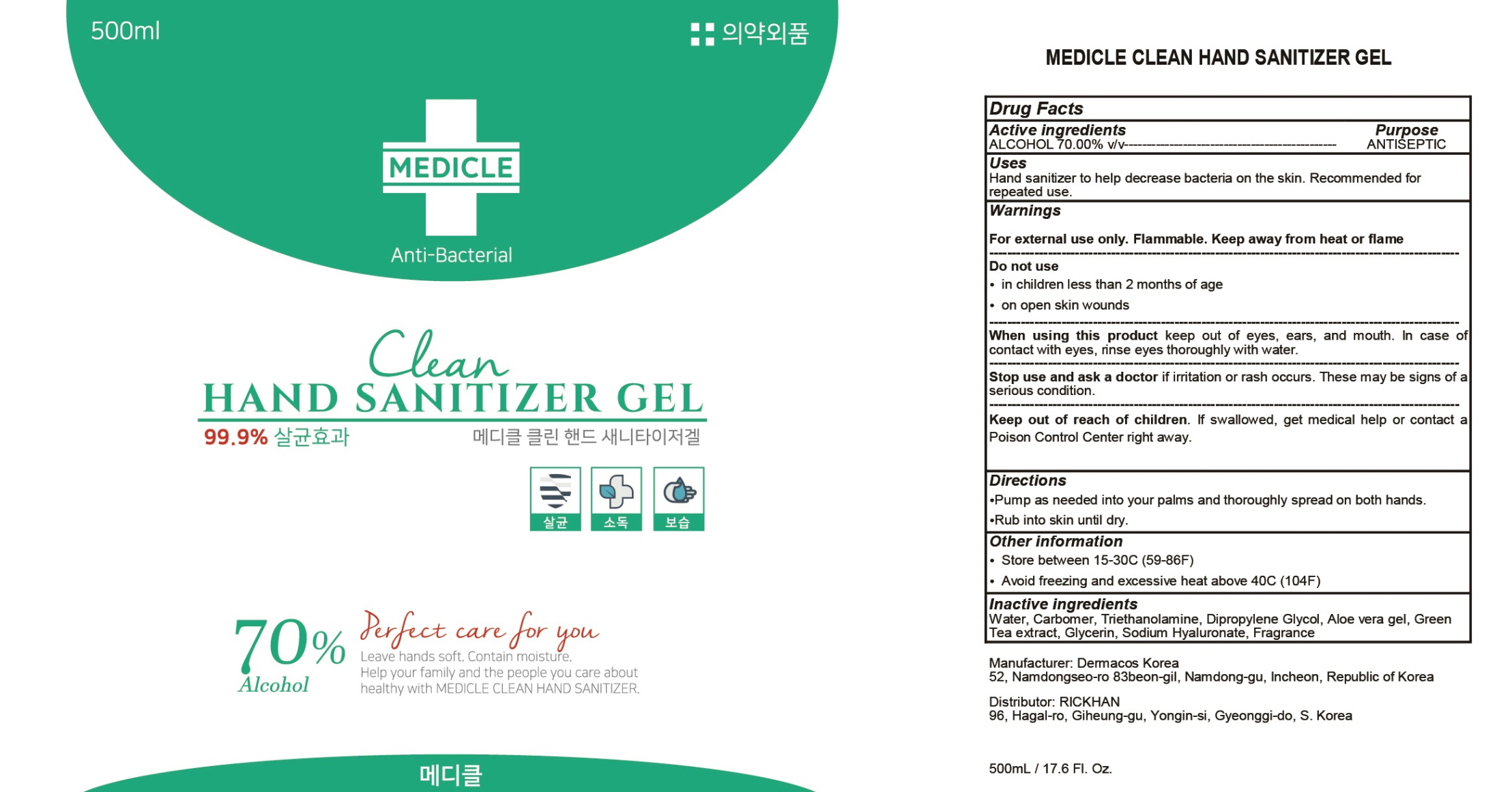 DRUG LABEL: MEDICLE CLEAN HAND SANITIZER
NDC: 76898-010 | Form: GEL
Manufacturer: RICKHAN
Category: otc | Type: HUMAN OTC DRUG LABEL
Date: 20200501

ACTIVE INGREDIENTS: ALCOHOL 350 mL/500 mL
INACTIVE INGREDIENTS: Water; CARBOMER HOMOPOLYMER, UNSPECIFIED TYPE; TROLAMINE; Dipropylene Glycol; ALOE VERA LEAF; GREEN TEA LEAF; Glycerin; HYALURONATE SODIUM

ACTIVE INGREDIENT

Active ingredients: ALCOHOL 70.00% v/v

INACTIVE INGREDIENT

Inactive ingredients:

Water, Carbomer, Triethanolamine, Dipropylene Glycol, Aloe vera gel, Green Tea extract, Glycerin, Sodium Hyaluronate, Fragrance

PURPOSE

Purpose: ANTISEPTIC

WARNINGS

For external use only. Flammable. Keep away from heat or flame
--------------------------------------------------------------------------------------------------------
Do not use
• in children less than 2 months of age
• on open skin wounds
--------------------------------------------------------------------------------------------------------
When using this product keep out of eyes, ears, and mouth. In case of contact with eyes, rinse eyes thoroughly with water.
--------------------------------------------------------------------------------------------------------
Stop use and ask a doctor if irritation or rash occurs. These may be signs of a serious condition.

KEEP OUT OF REACH OF CHILDREN

If swallowed, get medical help or contact a Poison Control Center right away.

Uses

Hand sanitizer to help decrease bacteria on the skin.

Recommended for repeated use.

Directions

• Pump as needed into your palms and thoroughly spread on both hands.
• Rub into skin until dry.

Other information

• Store between 15-30C (59-86F)
• Avoid freezing and excessive heat above 40C (104F)